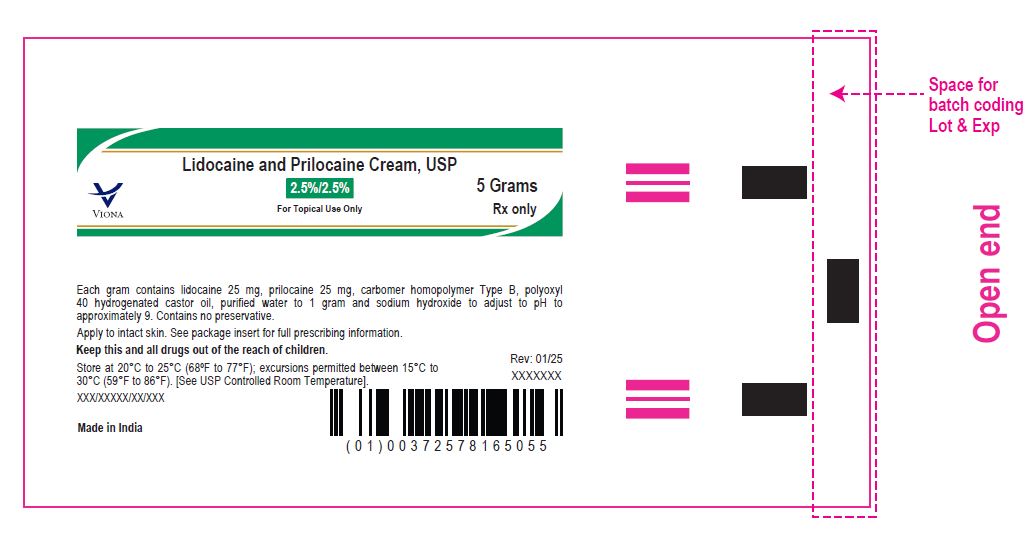 DRUG LABEL: Lidocaine and prilocaine
NDC: 70771-1872 | Form: CREAM
Manufacturer: Zydus Lifesciences Limited
Category: prescription | Type: HUMAN PRESCRIPTION DRUG LABEL
Date: 20241230

ACTIVE INGREDIENTS: LIDOCAINE 25 mg/1 g; PRILOCAINE 25 mg/1 g
INACTIVE INGREDIENTS: CARBOMER HOMOPOLYMER TYPE B (ALLYL PENTAERYTHRITOL CROSSLINKED); POLYOXYL 40 HYDROGENATED CASTOR OIL; SODIUM HYDROXIDE; WATER

Lidocaine and Prilocaine Cream USP, 2.5 %/2.5 %

PACKAGE LABEL.PRINCIPAL DISPLAY PANEL

NDC 70771-1872-5

Lidocaine and Prilocaine Cream USP, 2.5%/2.5%

5 grams

Rx